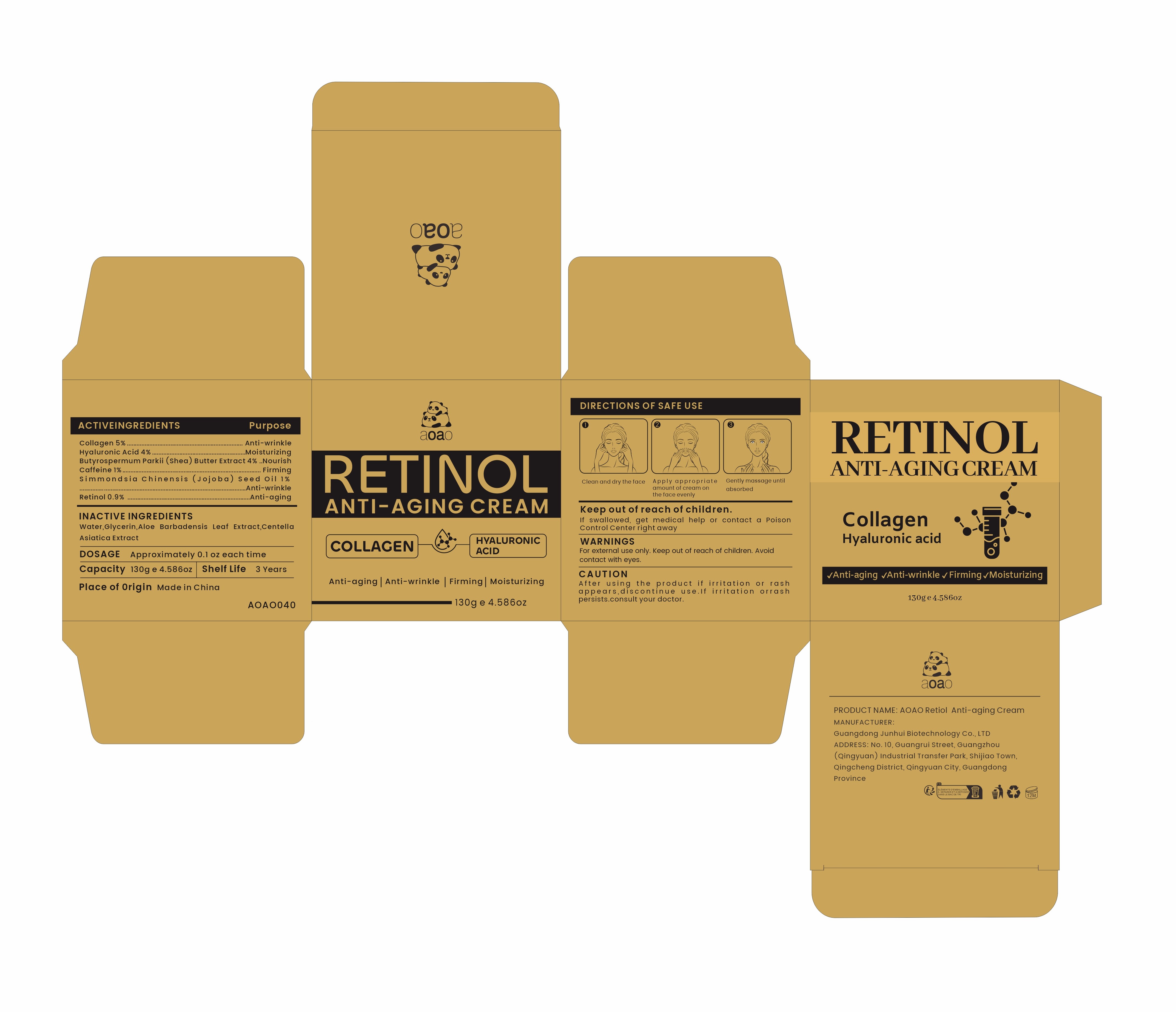 DRUG LABEL: AOAO Retiol Anti-aging Cream
NDC: 84509-038 | Form: CREAM
Manufacturer: Guangdong Junhui Biotechnology Co., LTD
Category: otc | Type: HUMAN OTC DRUG LABEL
Date: 20241106

ACTIVE INGREDIENTS: CAFFEINE 1300 mg/130 g; SIMMONDSIA CHINENSIS (JOJOBA) SEED OIL 1300 mg/130 g; RETINOL 1170 mg/130 g; BUTYROSPERMUM PARKII (SHEA) BUTTER EXTRACT 5200 mg/130 g; COLLAGEN, SOLUBLE, FISH SKIN 6500 mg/130 g; HYALURONIC ACID 5200 mg/130 g
INACTIVE INGREDIENTS: WATER; GLYCERIN; ALOE BARBADENSIS LEAF EXTRACT; CENTELLA ASIATICA TRITERPENOIDS

Active Ingredients

Collagen 5%
Butyrospermum Parkii (Shea) Butter Extract 4%
Hyaluronic Acid 4%
Caffeine 1%
Simmondsia Chinensis (Jojoba) Seed Oil 1%
Retinol 0.9%

Purpose

Anti-wrinkle
Nourish
Moisturizing
Firming
Anti-aging

Uses

1、Clean and dry the face
2、Apply an appropriateamount of face cream evenly on the face
3、Gently massage until absorbed

Warnings

For external use only. Keep out ofreach of children.Avoid contact with eyes

Keep out of reach of children

If swallowed, get medical help or contact a Poison Control Center right away

CAUTION

After using the product if irritation or rash appears,discontinue use.If irritation or
rash persists.consult your doctor.

Inactive Ingredients

Water,Glycerin,Aloe Barbadensis Leaf Extract，Centella Asiatica Extract

Product Name

AOAO Retiol Anti-aging Cream

DOSAGE

Approximately 0.1oz each time

Manufacturer

Guangdong Junhui Biotechnology Co., LTD

ADDRESS

No. 10, Guangrui Street, Guangzhou (Qingyuan) Industrial Transfer Park, Shijiao Town, Qingcheng District, Qingyuan City, Guangdong Province

Capacity

130 g e 4.586oz

Shelf Life

3 Years

Place of Origin

Made in China